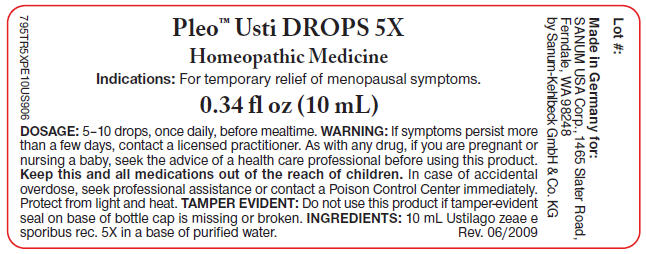 DRUG LABEL: Pleo Usti
NDC: 60681-5601 | Form: SOLUTION/ DROPS
Manufacturer: Sanum Kehlbeck GmbH & Co. KG
Category: homeopathic | Type: HUMAN OTC DRUG LABEL
Date: 20091125

ACTIVE INGREDIENTS: ustilago maydis 5 [hp_X]/10 mL
INACTIVE INGREDIENTS: water

Pleo™ Usti
DROPS 5X

Homeopathic Medicine

0.34 fl oz
(10 mL)

Indications

For temporary relief of menopausal symptoms.

INGREDIENTS

10 mL Ustilago zeae e sporibus rec. 5X in a base of purified water.

Tamper Evident

Do not use this product if tamper-evident seal on base of bottle cap is missing or broken.

DOSAGE

5–10 drops, once daily, before mealtime.

WARNING

If symptoms persist more than a few days, contact a licensed practitioner. As with any drug, if you are pregnant or nursing a baby, seek the advice of a health care professional before using this product.

KEEP OUT OF REACH OF CHILDREN

Keep this and all medications out of the reach of children. In case of accidental overdose, seek professional assistance or contact a Poison Control Center immediately.

STORAGE AND HANDLING

Protect from light and heat.

Made in Germany

Distributed by:
SANUM USA Corp.
1465 Slater Road
Ferndale, WA 98248

Manufactured By:
Sanum-Kehlbeck,
GmbH & Co. KG

Rev. 08/2005

PRINCIPAL DISPLAY PANEL - 10 mL Label

Pleo™ Usti DROPS 5X

Homeopathic Medicine

Indications: For temporary relief of menopausal symptoms.

0.34 fl oz (10 mL)

DOSAGE:5–10 drops, once daily, before mealtime. WARNING: If symptoms persist more
than a few days, contact a licensed practitioner. As with any drug, if you are pregnant or
nursing a baby, seek the advice of a health care professional before using this product.
Keep this and all medications out of the reach of children. In case of accidental
overdose, seek professional assistance or contact a Poison Control Center immediately.
Protect from light and heat. TAMPER EVIDENT: Do not use this product if tamper-evident
seal on base of bottle cap is missing or broken. INGREDIENTS: 10 mL Ustilago zeae e
sporibus rec. 5X in a base of purified water.
Rev. 06/2009